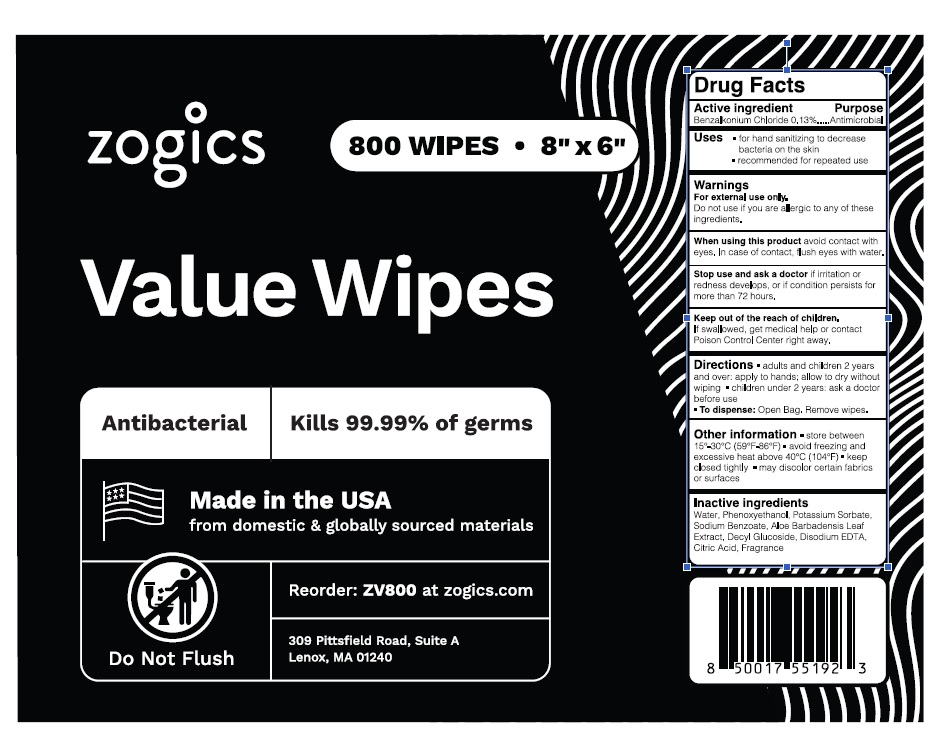 DRUG LABEL: Value Wipes
NDC: 72202-013 | Form: CLOTH
Manufacturer: Zogics, LLC
Category: otc | Type: HUMAN OTC DRUG LABEL
Date: 20241216

ACTIVE INGREDIENTS: BENZALKONIUM CHLORIDE 0.13 g/100 g
INACTIVE INGREDIENTS: WATER; PHENOXYETHANOL; DECYL GLUCOSIDE; POTASSIUM SORBATE; SODIUM BENZOATE; EDETATE DISODIUM; CITRIC ACID MONOHYDRATE; ALOE VERA LEAF

Drug Facts

Active ingredient

Benzalkonium chloride 0.13%

Purpose

Antimicrobial

Uses

- For hand sanitizing to decrease the bacteria on the skin
- recommended for repated use

Warnings

For external use only

Do not use if allergic to any of these ingredients.

When using this product

avoid contact with eyes. In case of contact, flush eyes with water.

Stop use and ask a doctor

If irritation or redness develops, or if condition persists for more than 72 hours.

Keep out of the reach of children

If swallowed, get medical help or contact a Poison Control Center immediately.

Directions

- adults and childrens 2 years and older apply to hands; allow to dry without wiping
- children under 2 years ask a doctor

To dispense: Open Bad, remove the wipe

Other information

- store between 15°-30°C (59°F-86°F)
- avoid freezing and excessive heat above 40°C (104°F)
- keep closed tightly
- may discolor certain fabrics or surfaces

Inactive ingredients

Water, Phenoxyethanol, Potassium Sorbate, Sodium Benzoate, Aloe Barbadensis (Aloe) Leaf Extract, Decyl Glucoside, Disodium EDTA, Citric Acid, Fragrance.

Principal Display Panel

NDC 72202-013-80

800 WIPES (8" X 6")

Zogic Value Wipes

Antibacterial Kills 99.99% of germs

Made in the USA from domestic & globally sourced materials

Reorder: ZV800 at zogics.com

DO NOT FLUSH
309 Pittsfield Road, Suite A, Lenox, MA 01240